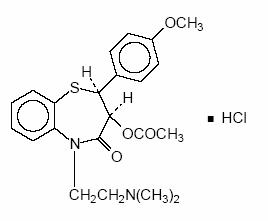 DRUG LABEL: Unknown
Manufacturer: Watson Laboratories Inc.
Category: prescription | Type: HUMAN PRESCRIPTION DRUG LABELING
Date: 20061009

Diltiazem Hydrochloride Extended Release Tablets
Issued: October 2005
Rx Only
Once-a-day dosage

DESCRIPTION

Diltiazem hydrochloride is a calcium ion cellular influx inhibitor (slow channel blocker or calcium antagonist). Chemically, diltiazem hydrochloride is 1,5-benzothiazepin-4(5H)one,3-(acetyloxy)-5-[2-(dimethylamino)ethyl]-2, 3-dihydro-2-(4-methoxyphenyl)-, monohydrochloride, (+)-cis-.

The structural formula is:

Diltiazem hydrochloride is a white to off-white crystalline powder with a bitter taste. It is soluble in water, methanol and chloroform. It has a molecular weight of 450.99. Diltiazem Hydrochloride Extended Release Tablets, for oral administration, are formulated as a once-a-day extended release tablet containing either120 mg, 180 mg, 240 mg, 300 mg, 360 mg or 420 mg of diltiazem hydrochloride.

Also contains: Monosodium Citrate Anhydrous Powder; Polyethylene Glycol, NF (PEG-6000); Povidone, USP; Magnesium Stearate, NF; Dehydrated Alcohol, USP; Lactose Monohydrate, NF; Acetyltributyl Citrate, NF; Sodium Bicarbonate, USP; Multipor® Coating Polymer; Titanium Dioxide, USP; Acetone, NF; Ethylcellulose, NF; Hypromellose, USP; Purified Water, USP; Talc, USP; Isopropyl Alcohol, USP; n-Butyl Alcohol, NF; Propylene Glycol, USP; Opacode Black Ink.

CLINICAL PHARMACOLOGY

The therapeutic effects of diltiazem are believed to be related to its ability to inhibit the influx of calcium ions during membrane depolarization of cardiac and vascular smooth muscle.

Mechanisms of Action

Hypertension

Diltiazem produces its antihypertensive effect primarily by relaxation of vascular smooth muscle and the resultant decrease in peripheral vascular resistance. The magnitude of blood pressure reduction is related to the degree of hypertension; thus hypertensive individuals experience an antihypertensive effect, whereas there is only a modest fall in blood pressure in normotensives.

Angina

Diltiazem has been shown to produce increases in exercise tolerance, probably due to its ability to reduce myocardial oxygen demand. This is accomplished via reductions in heart rate and systemic blood pressure at submaximal and maximal work loads. Diltiazem has been shown to be a potent dilator of coronary arteries, both epicardial and subendocardial. Spontaneous and ergovine-induced coronary artery spasms are inhibited by diltiazem.

In animal models, diltiazem interferes with the slow inward (depolarizing) current in excitable tissues. It causes excitation-contraction uncoupling in various myocardial tissues without changes in the configuration of the action potential. Diltiazem causes relaxation of coronary smooth muscle and dilation of both large and small coronary arteries at drug levels which cause little or no negative inotropic effect. The resultant increases in coronary blood flow (epicardial and subendocardial) occur in ischemic and non-ischemic models and are accompanied by dose-dependent decreases in systemic blood pressure and decreases in peripheral resistance.

Pharmacokinetics and Metabolism

Diltiazem is well absorbed from the gastrointestinal tract and is subject to an extensive first-pass effect, giving an absolute bioavailability (compared to intravenous administration) of about 40%. Diltiazem undergoes extensive metabolism in which only 2% to 4% of the unchanged drug appears in the urine. Drugs which induce or inhibit hepatic microsomal enzymes may alter diltiazem disposition.

Total radioactivity measurement following short IV administration in healthy volunteers suggests the presence of other unidentified metabolites, which attain higher concentrations than those of diltiazem and are more slowly eliminated; half-life of total radioactivity is about 20 hours compared to 2 to 5 hours for diltiazem.

In vitro binding studies show diltiazem is 70% to 80% bound to plasma proteins. Competitive in vitro ligand binding studies have also shown diltiazem hydrochloride binding is not altered by therapeutic concentrations of digoxin, hydrochlorothiazide, phenylbutazone, propranolol, salicylic acid, or warfarin. The plasma elimination half-life following single or multiple drug administration is approximately 3.0 to 4.5 hours. Desacetyl diltiazem is also present in the plasma at levels of 10% to 20% of the parent drug and is 25% to 50% as potent as a coronary vasodilator as diltiazem. Minimum therapeutic plasma diltiazem concentrations appear to be in the range of 50 to 200 ng/mL. There is a departure from linearity when dose strengths are increased; the half-life is slightly increased with dose. A study that compared patients with normal hepatic function to patients with cirrhosis found an increase in half-life and a 69% increase in bioavailability in the hepatically impaired patients. A single study in patients with severely impaired renal function showed no difference in the pharmacokinetic profile of diltiazem compared to patients with normal renal function.

Diltiazem Hydrochloride Extended Release Tablets

A single 360 mg dose of diltiazem results in detectable plasma levels within 3 to 4 hours and peak plasma levels between 11 and 18 hours; absorption occurs throughout the dosing interval. The apparent elimination half-life for diltiazem after single or multiple dosing is 6 to 9 hours. When Diltiazem Hydrochloride Extended Release Tablets were coadministered with a high fat content breakfast, diltiazem peak and systemic exposures were not affected indicating that the tablet can be administered without regard to food. As the dose of diltiazem is increased from 120 to 240 mg, area-under-the-curve increases 2.5-fold.

Pharmacodynamics and Clinical Studies

Like other calcium channel antagonists, diltiazem decreases sinoatrial and atrioventricular conduction in isolated tissues and has a negative inotropic effect in isolated preparations. In the intact animal, prolongation of the AH interval can be seen at higher doses.

In man, diltiazem prevents spontaneous and ergonovine-provoked coronary artery spasm. It causes a decrease in peripheral vascular resistance and a modest fall in blood pressure in normotensive individuals and, in exercise tolerance studies in patients with ischemic heart disease, reduces the heart rate-blood pressure product for any given work load. Studies to date, primarily in patients with good ventricular function, have not revealed evidence of a negative inotropic effect; cardiac output, ejection fraction, and left ventricular end diastolic pressure have not been affected. Such data has no predictive value with respect to effects in patients with poor ventricular function, and increased heart failure has been reported in patients with preexisting impairment of ventricular function. There are as yet few data on the interaction of diltiazem and beta-blockers in patients with poor ventricular function. Resting heart rate is usually slightly reduced by diltiazem. Diltiazem decreases vascular resistance, increases cardiac output (by increasing stroke volume), and produces a slight decrease or no change in heart rate.

During dynamic exercise, increases in diastolic pressure are inhibited, while maximum achievable systolic pressure is usually reduced. Chronic therapy with diltiazem produces no change or an increase in plasma catecholamines. No increased activity of the renin-angiotensin-aldosterone axis has been observed. Diltiazem reduces the renal and peripheral effects of angiotensin II. Hypertensive animal models respond to diltiazem with reductions in blood pressure and increased urinary output and natriuresis without a change in urinary sodium/potassium ratio.

Intravenous diltiazem hydrochloride in doses of 20 mg prolongs AH conduction time and AV node functional and effective refractory periods by approximately 20%. In a study involving single oral doses of 300 mg of diltiazem hydrochloride in six normal volunteers, the average maximum PR prolongation was 14% with no instances of greater than first-degree AV block. Diltiazem associated prolongation of the AH interval is not more pronounced in patients with first-degree heart block. In patients with sick sinus syndrome, diltiazem significantly prolongs sinus cycle length (up to 50% in some cases). Chronic oral administration of diltiazem hydrochloride to patients in doses of up to 540 mg/day has resulted in small increases in PR interval, and on occasion produces abnormal prolongation (See WARNINGS).

Hypertension

In a randomized, double-blind, parallel-group, dose-response study involving 478 patients with essential hypertension, evening doses of diltiazem 120, 240, 360, and 540 mg were compared to placebo and to 360 mg administered in the morning. The mean reductions in diastolic blood pressure by ABPM at roughly 24 hours after the morning (4 AM to 8AM) or evening (6 PM to 10 PM) administration (i.e., the time corresponding to expected trough serum concentrations) are shown in the table below:

Mean Change in Trough Diastolic Pressure by ABPM
Evening Dosing |  |  |  | Morning Dosing
120 mg | 240 mg | 360 mg | 540 mg | 360 mg
-2.0 | -4.4 | -4.4 | -8.1 | -6.4

A second randomized, double-blind, parallel-group, dose-response study (N=258) evaluated diltiazem following morning doses of placebo or 120, 180, 300, or 540 mg. Diastolic blood pressure measured by supine office cuff sphygmomanometer at trough (7 AM to 9 AM) decreased in an apparently linear manner over the dosage range studied. Group mean changes for placebo, 120 mg, 180 mg, 300 mg and 540 mg were -2.6, -1.9, -5.4, -6.1 and - 8.6 mm Hg respectively.

Whether the time of administration impacts the clinical benefits of antihypertensive treatment is not known.

Postural hypotension is infrequently noted upon suddenly assuming an upright position. No reflex tachycardia is associated with the chronic antihypertensive effects.

Angina

The effects of diltiazem on angina were evaluated in a randomized, double-blind, parallel-group, dose-response trial of 311 patients with chronic stable angina. Evening doses of 180, 360 and 420 mg were compared to placebo and to 360 mg administered in the morning. All doses of diltiazem administered at night increased exercise tolerance when compared with placebo after 21 hours. The mean effect, placebo-subtracted, was 20 to 28 seconds for all three doses, and no dose-response was demonstrated. Diltiazem Hydrochloride Extended Release Tablet, 360 mg, given in the morning, also improved exercise tolerance when measured 25 hours later. As expected, the effect was smaller than the effects measured only 21 hours following nighttime administration. Diltiazem had a larger effect to increase exercise tolerance at peak serum concentrations than at trough.

INDICATIONS AND USAGE

Diltiazem Hydrochloride Extended Release Tablets are indicated for the treatment of hypertension. It may be used alone or in combination with other antihypertensive medications. Diltiazem Hydrochloride Extended Release Tablets are indicated for the management of chronic stable angina.

CONTRAINDICATIONS

Diltiazem is contraindicated in (1) patients with sick sinus syndrome except in the presence of a functioning ventricular pacemaker, (2) patients with second- or third-degree AV block except in the presence of a functioning ventricular pacemaker, (3) patients with hypotension (less than 90 mm Hg systolic), (4) patients who have demonstrated hypersensitivity to the drug, and (5) patients with acute myocardial infarction and pulmonary congestion documented by x-ray on admission.

WARNINGS

Cardiac Conduction

Diltiazem prolongs AV node refractory periods without significantly prolonging sinus node recovery time, except in patients with sick sinus syndrome. This effect may rarely result in abnormally slow heart rates (particularly in patients with sick sinus syndrome) or second- or third-degree AV block (13 of 3290 patients or 0.40%). Concomitant use of diltiazem with beta-blockers or digitalis may result in additive effects on cardiac conduction. A patient with Prinzmetal's angina developed periods of asystole (2 to 5 seconds) after a single dose of 60 mg of diltiazem (see ADVERSE REACTIONS section).

Congestive Heart Failure

Although diltiazem has a negative inotropic effect in isolated animal tissue preparations, hemodynamic studies in humans with normal ventricular function have not shown a reduction in cardiac index nor consistent negative effects on contractility (dp/dt). An acute study of oral diltiazem in patients with impaired ventricular function (ejection fraction 24% ± 6%) showed improvement in indices of ventricular function without significant decrease in contractile function (dp/dt). Worsening of congestive heart failure has been reported in patients with preexisting impairment of ventricular function. Experience with the use of diltiazem in combination with betablockers in patients with impaired ventricular function is limited. Caution should be exercised when using this combination.

Hypotension

Decreases in blood pressure associated with diltiazem therapy may occasionally result in symptomatic hypotension.

Acute Hepatic Injury

Mild elevations of transaminases with and without concomitant elevation in alkaline phosphatase and bilirubin have been observed in clinical studies. Such elevations were usually transient and frequently resolved even with continued diltiazem treatment. In rare instances, significant elevations in enzymes such as alkaline phosphatase, LDH, SGOT, SGPT, and other phenomena consistent with acute hepatic injury have been noted. These reactions tended to occur early after therapy initiation (1 to 8 weeks) and have been reversible upon discontinuation of drug therapy. The relationship to diltiazem is uncertain in some cases, but probable in some (See PRECAUTIONS).

PRECAUTIONS

General

Diltiazem hydrochloride is extensively metabolized by the liver and excreted by the kidneys and in bile. As with any drug given over prolonged periods, laboratory parameters of renal and hepatic function should be monitored at regular intervals. The drug should be used with caution in patients with impaired renal or hepatic function.

In subacute and chronic dog and rat studies designed to produce toxicity, high doses of diltiazem were associated with hepatic damage. In special subacute hepatic studies, oral doses of 125 mg/kg and higher in rats were associated with histological changes in the liver, which were reversible when the drug was discontinued. In dogs, doses of 20 mg/kg were also associated with hepatic changes; however, these changes were reversible with continued dosing.

Dermatological events (see ADVERSE REACTIONS section) may be transient and may disappear despite continued use of diltiazem. However, skin eruptions progressing to erythema multiforme and/or exfoliative dermatitis have also been infrequently reported. Should a dermatologic reaction persist, the drug should be discontinued.

Drug interactions

Due to the potential for additive effects, caution and careful titration are warranted in patients receiving diltiazem concomitantly with other agents known to affect cardiac contractility and/or conduction (See WARNINGS). Pharmacologic studies indicate that there may be additive effects in prolonging AV conduction when using beta-blockers or digitalis concomitantly with diltiazem (See WARNINGS).

As with all drugs, care should be exercised when treating patients with multiple medications. Diltiazem is both a substrate and an inhibitor of the cytochrome P-450 3A4 enzyme system. Other drugs that are specific substrates, inhibitors, or inducers of this enzyme system may have a significant impact on the efficacy and side effect profile of diltiazem. Patients taking other drugs that are substrates of CYP450, especially patients with renal and/or hepatic impairment, may require dosage adjustment when starting or stopping concomitantly administered diltiazem in order to maintain optimum therapeutic blood levels.

Beta-Blockers

Controlled and uncontrolled domestic studies suggest that concomitant use of diltiazem and beta-blockers is usually well tolerated, but available data are not sufficient to predict the effects of concomitant treatment in patients with left ventricular dysfunction or cardiac conduction abnormalities.

Administration of diltiazem concomitantly with propranolol in five normal volunteers resulted in increased propranolol levels in all subjects and bioavailability of propranolol was increased approximately 50%. In vitro, propranolol appears to be displaced from its binding sites by diltiazem. If combination therapy is initiated or withdrawn in conjunction with propranolol, an adjustment in the propranolol dose may be warranted (See WARNINGS).

Cimetidine

A study in six healthy volunteers has shown a significant increase in peak diltiazem plasma levels (58%) and area-under-the-curve (53%) after a 1-week course of cimetidine at 1200 mg per day and a single dose of diltiazem 60 mg. Ranitidine produced smaller, nonsignificant increases. The effect may be mediated by cimetidine's known inhibition of hepatic cytochrome P-450, the enzyme system responsible for the first-pass metabolism of diltiazem. Patients currently receiving diltiazem therapy should be carefully monitored for a change in pharmacological effect when initiating and discontinuing therapy with cimetidine. An adjustment in the diltiazem dose may be warranted.

Digitalis

Administration of diltiazem with digoxin in 24 healthy male subjects increased plasma digoxin concentrations approximately 20%. Another investigator found no increase in digoxin levels in 12 patients with coronary artery disease. Since there have been conflicting results regarding the effect of digoxin levels, it is recommended that digoxin levels be monitored when initiating, adjusting, and discontinuing diltiazem therapy to avoid possible over or under-digitalization (See WARNINGS).

Anesthetics

The depression of cardiac contractility, conductivity, and automaticity as well as the vascular dilation associated with anesthetics may be potentiated by calcium channel blockers. When used concomitantly, anesthetics and calcium blockers should be titrated carefully.

Benzodiazepines

Studies showed that diltiazem increased the AUC of midazolam and triazolam by 3- to 4-fold and the Cmax by 2-fold, compared to placebo. The elimination half-life of midazolam and triazolam also increase (1.5 to 2.5 fold) during coadministration with diltiazem. These pharmacokinetic effects seen during diltiazem coadministration can result in increased clinical effects (e.g., prolonged sedation) of both midazolam and triazolam.

Cyclosporine

A pharmacokinetic interaction between diltiazem and cyclosporine has been observed during studies involving renal and cardiac transplant patients. In renal and cardiac transplant recipients, a reduction of cyclosporine dose ranging from 15% to 48% was necessary to maintain cyclosporine trough concentrations similar to those seen prior to the addition of diltiazem. If these agents are to be administered concurrently, cyclosporine concentrations should be monitored, especially when diltiazem therapy is initiated, adjusted, or discontinued.

The effect of cyclosporine on diltiazem plasma concentrations has not been evaluated.

Carbamazepine

Concomitant administration of diltiazem with carbamazepine has been reported to result in elevated serum levels of carbamazepine (40% to 72% increase), resulting in toxicity in some cases. Patients receiving these drugs concurrently should be monitored for a potential drug interaction.

Lovastatin

In a ten-subject study, coadministration of diltiazem (120 mg bid diltiazem SR) with lovastatin resulted in a 3 to 4 times increase in mean lovastatin AUC and Cmax versus lovastatin alone; no change in pravastatin AUC and Cmax was observed during diltiazem coadministration. Diltiazem plasma levels were not significantly affected by lovastatin or pravastatin.

Rifampin

Coadministration of rifampin with diltiazem lowered the diltiazem plasma concentrations to undetectable levels. Coadministration of diltiazem with rifampin or any known CYP 3A4 inducer should be avoided when possible, and alternative therapy considered.

Carcinogenesis, mutagenesis, impairment of fertility

A 24-month study in rats at oral dosage levels of up to 100 mg/kg/day, and a 21-month study in mice at oral dosage levels of up to 30 mg/kg/day showed no evidence of carcinogenicity. There was also no mutagenic response in vitro or in vivo in mammalian cell assays or in vitro in bacteria. No evidence of impaired fertility was observed in a study performed in male and female rats at oral dosages of up to 100 mg/kg/day.

Pregnancy

Category C. Reproduction studies have been conducted in mice, rats, and rabbits. Administration of doses ranging from 4 to 6 times (depending on species) the upper limit of the optimum dosage range in clinical trials (480 mg q.d. or 8 mg/kg q.d. for a 60 kg patient) resulted in embryo and fetal lethality. These studies revealed, in one species or another, a propensity to cause fetal abnormalities of the skeleton, heart, retina, and tongue. Also observed were reductions in early individual pup weights, pup survival, as well as prolonged delivery times and an increased incidence of stillbirths. There are no well-controlled studies in pregnant women; therefore, use diltiazem in pregnant women only if the potential benefit justifies the potential risk to the fetus.

Nursing mothers

Diltiazem is excreted in human milk. One report suggests that concentrations in breast milk may approximate serum levels. If use of diltiazem is deemed essential, an alternative method of infant feeding should be instituted.

Pediatric use

Safety and effectiveness in pediatric patients have not been established.

Geriatric use

Clinical studies of diltiazem did not include sufficient numbers of subjects aged 65 and over to determine whether they respond differently from younger subjects. Other reported clinical experience has not identified differences in responses between the elderly and younger patients. In general, dose selection for an elderly patient should be cautious, usually starting at the low end of the dosing range, reflecting the greater frequency of decreased hepatic, renal, or cardiac function, and of concomitant disease or other drug therapy.

ADVERSE REACTIONS

Serious adverse reactions have been rare in studies carried out to date, but it should be recognized that patients with impaired ventricular function and cardiac conduction abnormalities have usually been excluded from these studies. In the hypertension study, the following table presents adverse reactions more common on diltiazem than on placebo (but excluding events with no plausible relationship to treatment), as reported in placebo-controlled hypertension trials in patients receiving a diltiazem hydrochloride extended-release formulation (once-a-day dosing) up to 540 mg.

Adverse Reactions (MedDRA Term) | Placebo | Diltiazem hydrochloride extended-release
Adverse Reactions (MedDRA Term) | n = 120 # pts (%) | 120–360 mg n = 501 # pts (%) | 540 mg n = 123 # pts (%)
Edema lower limb | 4 (3) | 24 (5) | 10 (8)
Sinus congestion | 0 (0) | 2 (1) | 2 (2)
Rash NOS | 0 (0) | 3 (1) | 2 (2)

In the angina study, the adverse event profile of Diltiazem Hydrochloride Extended Release Tablets was consistent with what has been previously described for Diltiazem Hydrochloride Extended Release Tablets and other formulations of diltiazem HCl. The most frequent adverse effects experienced by Diltiazem Hydrochloride Extended Release Tablet -treated patients were edema lower-limb (6.8%), dizziness (6.4%), fatigue (4.8%), bradycardia (3.6%), first-degree atrioventricular block (3.2%), and cough (2%).

In clinical trials of other diltiazem formulations involving over 3200 patients, the most common events (i.e. greater than 1%) were edema (4.6%), headache (4.6%), dizziness (3.5%), asthenia (2.6%), first-degree AV block (2.4%), bradycardia (1.7%), flushing (1.4%), nausea (1.4%) and rash (1.2%). In addition, the following events have been reported infrequently (less than 2%) in hypertension trials with other diltiazem products:

Cardiovascular: Angina, arrhythmia, AV block (second- or third-degree), bundle branch block, congestive heart failure, ECG abnormalities, hypotension, palpitations, syncope, tachycardia, ventricular extrasystoles.

Nervous System: Abnormal dreams, amnesia, depression, gait abnormality, hallucinations, insomnia, nervousness, paresthesia, personality change, somnolence, tinnitus, tremor.

Gastrointestinal: Anorexia, constipation, diarrhea, dry mouth, dysgeusia, mild elevations of SGOT, SGPT, LDH, and alkaline phosphatase (see hepatic warnings), nausea, thirst, vomiting, weight increase.

Dermatological: Petechiae, photosensitivity, pruritus.

Other: Albuminuria, allergic reaction, amblyopia, asthenia, CPK increase, crystalluria, dyspnea, ecchymosis, edema, epistaxis, eye irritation, headache, hyperglycemia, hyperuricemia, impotence, muscle cramps, nasal congestion, neck rigidity, nocturia, osteoarticular pain, pain, polyuria, rhinitis, sexual difficulties, gynecomastia.

The following postmarketing events have been reported infrequently in patients receiving diltiazem: allergic reactions, alopecia, angioedema (including facial or periorbital edema), asystole, erythema multiforme (including Stevens-Johnson syndrome, toxic epidermal necrolysis), exfoliative dermatitis, extrapyramidal symptoms, gingival hyperplasia, hemolytic anemia, increased bleeding time, leukopenia, purpura, retinopathy, and thrombocytopenia. In addition, events such as myocardial infarction have been observed which are not readily distinguishable from the natural history of the disease in these patients. A number of well-documented cases of generalized rash, some characterized as leukocytoclastic vasculitis, have been reported. However, a definitive cause and effect relationship between these events and diltiazem therapy is yet to be established.

OVERDOSAGE

The oral LD50's in mice and rats range from 415 to 740 mg/kg and from 560 to 810 mg/kg, respectively. The intravenous LD50's in these species were 60 and 38 mg/kg, respectively. The oral LD50 in dogs is considered to be in excess of 50 mg/kg, while lethality was seen in monkeys at 360 mg/kg.

The toxic dose in man is not known. Due to extensive metabolism, blood levels after a standard dose of diltiazem can vary over tenfold, limiting the usefulness of blood levels in overdose cases.

There have been 29 reports of diltiazem overdose in doses ranging from less than 1 g to 10.8 g. Sixteen of these reports involved multiple drug ingestions.

Twenty-two reports indicated patients had recovered from diltiazem overdose ranging from less than 1 g to 10.8 g. There were seven reports with a fatal outcome; although the amount of diltiazem ingested was unknown, multiple drug ingestions were confirmed in six of the seven reports.

Events observed following diltiazem overdose included bradycardia, hypotension, heart block, and cardiac failure. Most reports of overdose described some supportive medical measure and/or drug treatment. Bradycardia frequently responded favorably to atropine as did heart block, although cardiac pacing was also frequently utilized to treat heart block. Fluids and vasopressors were used to maintain blood pressure, and in cases of cardiac failure, inotropic agents were administered. In addition, some patients received treatment with ventilatory support, gastric lavage, activated charcoal, and/or intravenous calcium. Evidence of the effectiveness of intravenous calcium administration to reverse the pharmacological effects of diltiazem overdose was conflicting.

In the event of overdose or exaggerated response, appropriate supportive measures should be employed in addition to gastrointestinal decontamination. Diltiazem does not appear to be removed by peritoneal or hemodialysis. Limited data suggest that plasmapheresis or charcoal hemoperfusion may hasten diltiazem elimination following overdose. Based on the known pharmacological effects of diltiazem and/or reported clinical experiences, the following measures may be considered:

Bradycardia: Administer atropine (0.60 to 1 mg). If there is no response to vagal blockage, administer isoproterenol cautiously.

High-Degree AV Block: Treat as for bradycardia above. Fixed high-degree AV block should be treated with cardiac pacing.

Cardiac Failure: Administer inotropic agents (isoproterenol, dopamine, or dobutamine) and diuretics.

Hypotension: Vasopressors (e.g., dopamine or norepinephrine). Actual treatment and dosage should depend on the severity of the clinical situation and the judgment and experience of the treating physician.

DOSAGE AND ADMINISTRATION

Diltiazem Hydrochloride Extended Release Tablets are an extended release formulation intended for once-a-day administration.

Patients controlled on diltiazem alone or in combination with other medications may be switched to Diltiazem Hydrochloride Extended Release Tablets once-a-day at the nearest equivalent total daily dose. Higher doses of Diltiazem Hydrochloride Extended Release Tablets once-a-day dosage may be needed in some patients. Patients should be closely monitored. Subsequent titration to higher or lower doses may be necessary and should be initiated as clinically warranted. There is limited general clinical experience with doses above 360 mg, but the safety and efficacy of doses as high as 540 mg have been studied in clinical trials. The incidence of side effects increases as the dose increases with first-degree AV block, dizziness, and sinus bradycardia bearing the strongest relationship to dose.

The tablet should be swallowed whole and not chewed or crushed.

Hypertension

Dosage needs to be adjusted by titration to individual patient needs. When used as monotherapy, reasonable starting doses are 180 to 240 mg once daily, although some patients may respond to lower doses. Maximum antihypertensive effect is usually observed by 14 days of chronic therapy; therefore, dosage adjustments should be scheduled accordingly. The dosage range studied in clinical trials was 120 to 540 mg once daily. The dosage may be titrated to a maximum of 540 mg daily.

Diltiazem Hydrochloride Extended Release Tablets should be taken
about the same time once each day either in the morning or at bedtime. The time of dosing should be considered when making dose adjustments based on trough effects.

Angina

Dosage for the treatment of angina should be individualized based on response. The initial dose of 180 mg once daily may be increased at intervals of 7 to14 days if adequate response is not obtained. Diltiazem doses above 360 mg appear to confer no additional benefit. Diltiazem Hydrochloride Extended Release Tablet can be given once daily, either in the evening or in the morning.

Concomitant Use with Other Cardiovascular Agents

1. Sublingual NTG. May be taken as required to abort acute anginal attacks during Diltiazem Hydrochloride Extended-release therapy.
2. Prophylactic Nitrate Therapy. Diltiazem Hydrochloride Extended Release Tablets may be safely coadministered with short-and long-acting nitrates.
3. Beta-blockers. (See WARNINGS and PRECAUTIONS.)
4. Antihypertensives. Diltiazem has an additive antihypertensive effect when used with other antihypertensive agents. Therefore, the dosage of Diltiazem Hydrochloride Extended Release Tablets or the concomitant antihypertensives may need to be adjusted when adding one to the other.

HOW SUPPLIED

Diltiazem Hydrochloride Extended Release Tablets are supplied as:

120 mg: white to off-white round tablets imprinted with “WPI” over “3360” in black ink, supplied in bottles of 30, 90 and 1000.

180 mg: white to off-white round tablets imprinted with “WPI” over “3361” in black ink, supplied in bottles of 30, 90 and 1000.

240 mg: white to off-white round tablets imprinted with “WPI” over “3362” in black ink, supplied in bottles of 30, 90 and 1000.

300 mg: white to off-white round tablets imprinted with “WPI” over “3368” in black ink, supplied in bottles of 30, 90 and 1000.

360 mg: white to off-white round tablets imprinted with “WPI” over “3363” in black ink, supplied in bottles of 30, 90 and 1000.

420 mg: white to off-white round tablets imprinted with “WPI” over “3364” in black ink, supplied in bottles of 30, 90 and 1000.

Store at 20° to 25°C (68° to 77°F). [See USP Controlled Room Temperature.]

Avoid excessive humidity and temperatures above 30°C (86°F).

Dispense in tight, light resistant container as defined in USP.

Rx Only.

Watson Laboratories Inc.

Corona, CA 92880 USA

Rev. October 2005